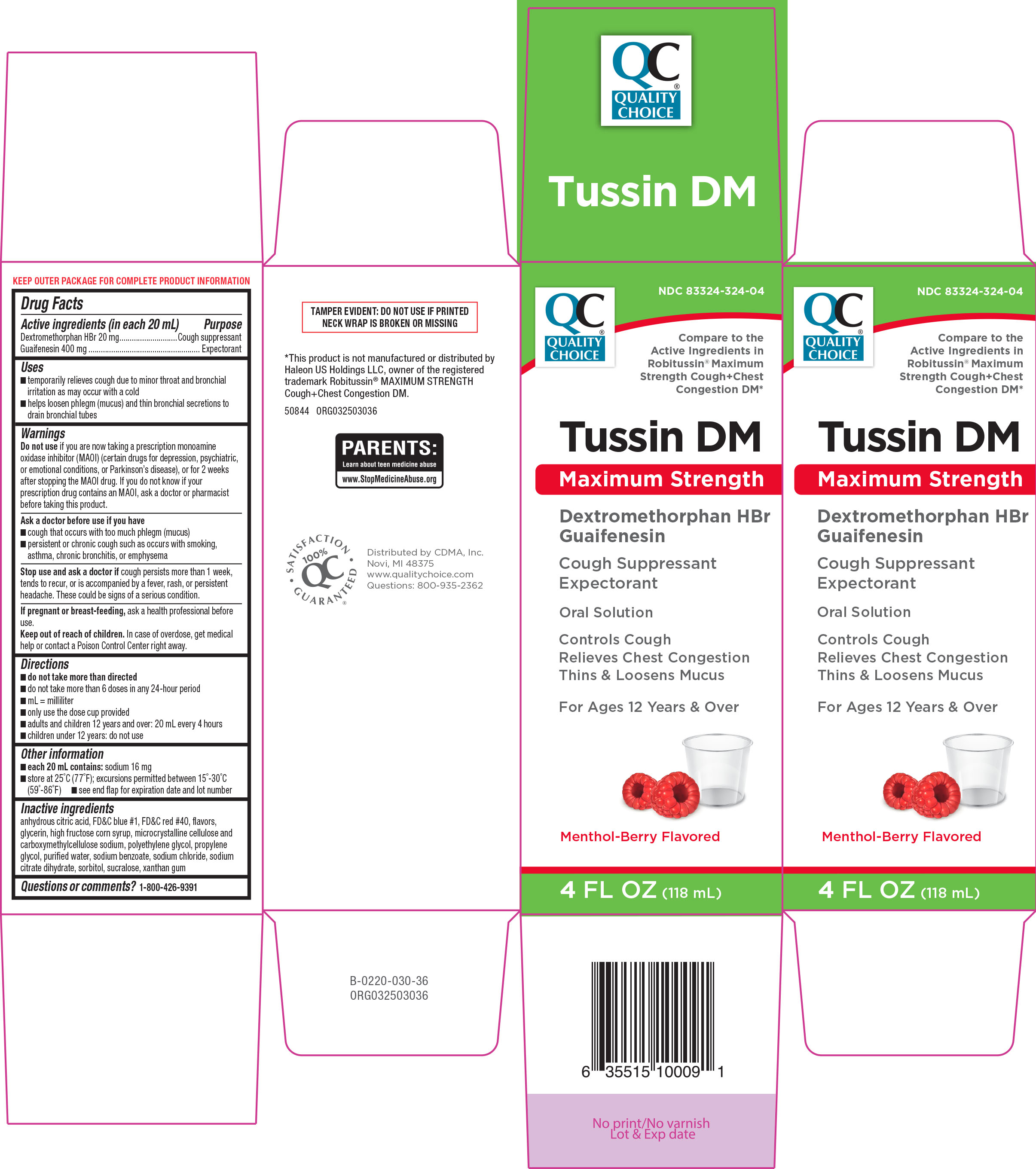 DRUG LABEL: Tussin DM
NDC: 83324-324 | Form: SOLUTION
Manufacturer: Chain Drug Marketing Association, Inc.
Category: otc | Type: HUMAN OTC DRUG LABEL
Date: 20250902

ACTIVE INGREDIENTS: DEXTROMETHORPHAN HYDROBROMIDE 20 mg/20 mL; GUAIFENESIN 400 mg/20 mL
INACTIVE INGREDIENTS: ANHYDROUS CITRIC ACID; FD&C BLUE NO. 1; FD&C RED NO. 40; GLYCERIN; HIGH FRUCTOSE CORN SYRUP; MICROCRYSTALLINE CELLULOSE; CARBOXYMETHYLCELLULOSE SODIUM, UNSPECIFIED; POLYETHYLENE GLYCOL, UNSPECIFIED; PROPYLENE GLYCOL; WATER; SODIUM BENZOATE; SODIUM CHLORIDE; TRISODIUM CITRATE DIHYDRATE; SORBITOL; SUCRALOSE; XANTHAN GUM

Quality Choice 44-030

Active ingredients (in each 20 mL)

Dextromethorphan HBr 20 mg
Guaifenesin 400 mg

Purpose

Cough suppressant
Expectorant

Uses

- temporarily relieves cough due to minor throat and bronchial irritation as may occur with a cold
- helps loosen phlegm (mucus) and thin bronchial secretions to drain bronchial tubes

Warnings

Do not use

if you are now taking a prescription monoamine oxidase inhibitor (MAOI) (certain drugs for depression, psychiatric or emotional conditions, or Parkinson's disease), or for 2 weeks after stopping the MAOI drug. If you do not know if your prescription drug contains an MAOI, ask a doctor or pharmacist before taking this product.

Ask a doctor before use if you have

- cough that occurs with too much phlegm (mucus)
- persistent or chronic cough such as occurs with smoking, asthma, chronic bronchitis, or emphysema

Stop use and ask a doctor if

cough persists more than 7 days, tends to recur, or is accompanied by a fever, rash, or persistent headache. These could be signs of a serious condition.

If pregnant or breast-feeding,

ask a health professional before use.

Keep out of reach of children.

In case of overdose, get medical help or contact a Poison Control Center right away.

Directions

- do not take more than directed
- do not take more than 6 doses in any 24-hour period
- mL = milliliter
- only use the dose cup provided
- adults and children 12 years and over: 20 mL in dosing cup provided every 4 hours
- children under 12 years: do not use

Other information

- each 20 mL contains: sodium 16 mg
- store at 25°C (77°F); excursions permitted between 15°-30°C (59°-86°F)
- see end flap for expiration date and lot number

Inactive ingredients

anhydrous citric acid, FD&C blue #1, FD&C red #40, flavors, glycerin, high fructose corn syrup, microcrystalline cellulose, polyethylene glycol, propylene glycol, purified water, sodium benzoate, sodium chloride, sodium citrate dihydrate, sorbitol, sucralose, xanthan gum

Questions or comments?

1-800-426-9391

Principal Display Panel

QC
Quality
Choice ®

NDC 83324-324-04

Compare to the
Active Ingredients in
Robitussin® Maximum
Strength Cough+Chest
Congestion DM*

Tussin DM

Maximum Strength

Dextromethorphan HBr
Guaifenesin
Cough Suppressant
Expectorant

Oral Solution

Controls Cough
Relieves Chest Congestion
Thins & Loosens Mucus

For Ages 12 Years & Over

Menthol-Berry Flavored

4 FL OZ (118 mL)

TAMPER EVIDENT: DO NOT USE IF PRINTED
NECK WRAP IS BROKEN OR MISSING

*This product is not manufactured or distributed by
Haleon US Holdings LLC, owner of the registered
trademark Robitussin® MAXIMUM STRENGTH
Cough+Chest Congestion DM.

50844 ORG032503036

Distributed by CDMA, Inc.
Novi, MI 48375
www.qualitychoice.com
Questions: 800-935-2362

Quality Choice 44-030